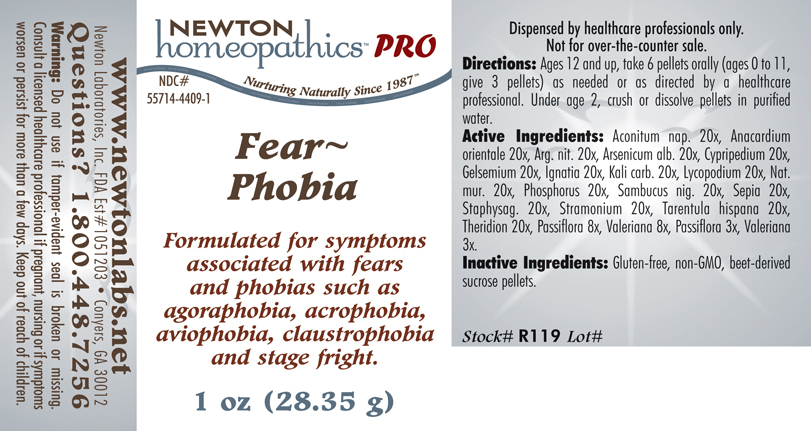 DRUG LABEL: Fear Phobia 
NDC: 55714-4409 | Form: PELLET
Manufacturer: Newton Laboratories, Inc.
Category: homeopathic | Type: HUMAN PRESCRIPTION DRUG LABEL
Date: 20110601

ACTIVE INGREDIENTS: Aconitum Napellus 20 [hp_X]/1 g; Semecarpus Anacardium Juice 20 [hp_X]/1 g; Silver Nitrate 20 [hp_X]/1 g; Arsenic Trioxide 20 [hp_X]/1 g; Cypripedium Parvifolum Root 20 [hp_X]/1 g; Gelsemium Sempervirens Root 20 [hp_X]/1 g; Strychnos Ignatii Seed 20 [hp_X]/1 g; Potassium Carbonate 20 [hp_X]/1 g; Lycopodium Clavatum Spore 20 [hp_X]/1 g; Sodium Chloride 20 [hp_X]/1 g; Phosphorus 20 [hp_X]/1 g; Sambucus Nigra Flowering Top 20 [hp_X]/1 g; Sepia Officinalis Juice 20 [hp_X]/1 g; Delphinium Staphisagria Seed 20 [hp_X]/1 g; Datura Stramonium 20 [hp_X]/1 g; Lycosa Tarantula 20 [hp_X]/1 g; Theridion Curassavicum 20 [hp_X]/1 g; Passiflora Incarnata Flowering Top 8 [hp_X]/1 g; Valerian 8 [hp_X]/1 g
INACTIVE INGREDIENTS: Sucrose

Fear Phobia

INDICATIONS & USAGE SECTION

Fear~Phobia Formulated for symptoms associated with fears and phobias such as agoraphobia, acrophobia, aviophobia, claustrophobia and stage fright.

DOSAGE & ADMINISTRATION SECTION

Ages 12 and up, take 6 pellets orally (ages 0 to 11, give 3 pellets) as needed or as directed by a healthcare professional. Under age 2, crush or dissolve pellets in purified water.

ACTIVE INGREDIENT SECTION

Aconitum nap. 20x, Anacardium orientale 20x, Arg. nit. 20x, Arsenicum alb. 20x, Cypripedium 20x,Gelsemium 20x, Ignatia 20x, Kali carb. 20x, Lycopodium 20x, Nat.mur. 20x, Phosphorus 20x, Sambucus nig. 20x, Sepia 20x, Staphysag. 20x, Stramonium 20x, Tarentula hispana 20x, Theridion 20x, Passiflora 8x, Valeriana 8x, Passiflora 3x, Valeriana 3x.

PURPOSE SECTION

Formulated for symptoms associated with fears and phobias such as agoraphobia, acrophobia, aviophobia, claustrophobia and stage fright.

INACTIVE INGREDIENT SECTION

Inactive Ingredients: Gluten-free, non-GMO, beet-derived sucrose pellets.

QUESTIONS? SECTION

www.newtonlabs.net Newton Laboratories, Inc. FDA Est # 1051203 - Conyers, GA 30012
Questions? 1.800.448.7256

WARNINGS SECTION

Warning: Do not use if tamper - evident seal is broken or missing. Consult a licensed healthcare professional if pregnant, nursing or if symptoms worsen or persist for more than a few days. Keep out of reach of children.

PREGNANCY OR BREAST FEEDING SECTION

Consult a licensed healthcare professional if pregnant, nursing or if symptoms worsen or persist for more than a few days.

KEEP OUT OF REACH OF CHILDREN SECTION

Keep out of reach of children.